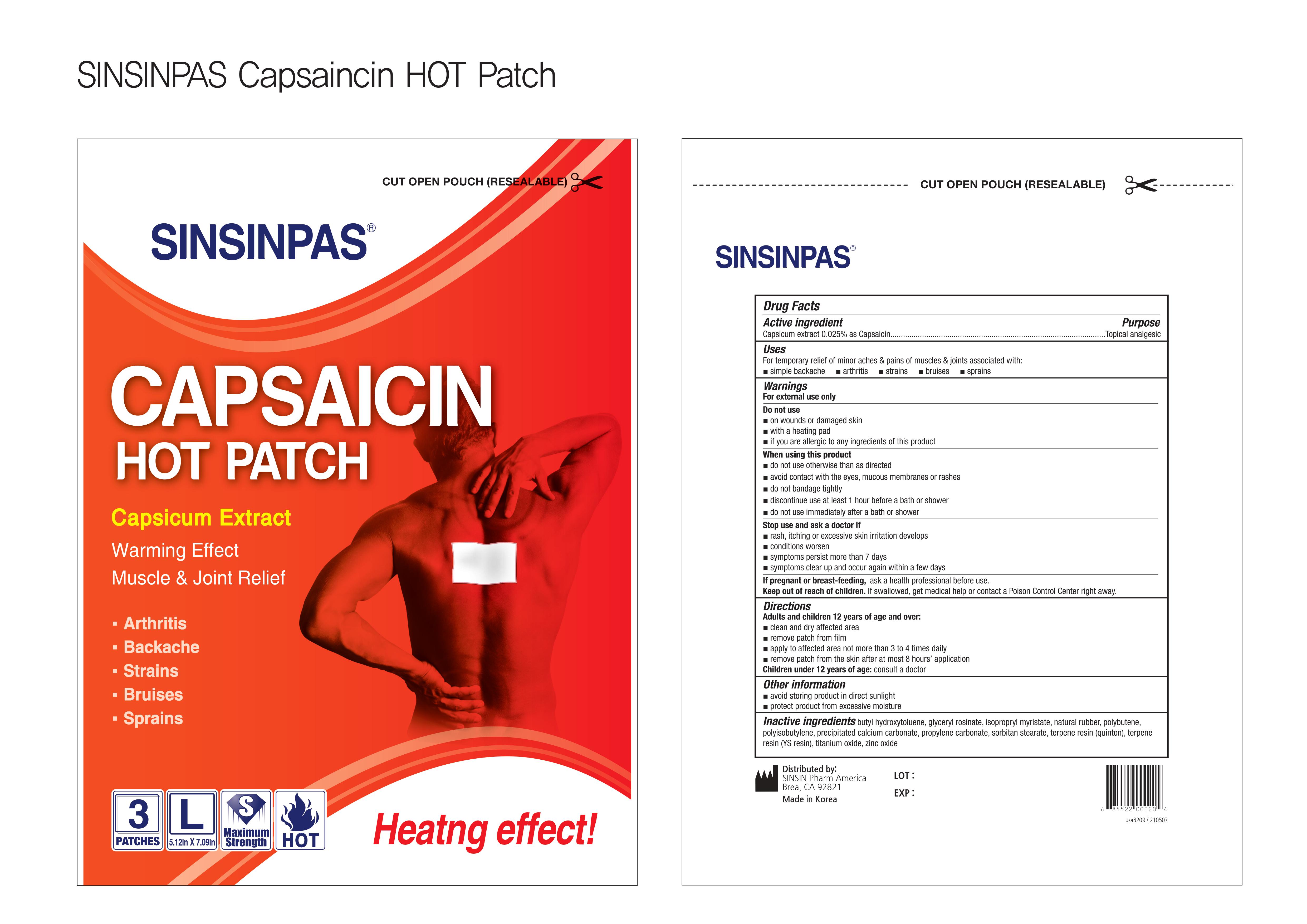 DRUG LABEL: SINSINPAS HOT LARGE
NDC: 55264-110 | Form: PATCH
Manufacturer: Sinsin Pharmaceutical Co., Ltd.
Category: otc | Type: HUMAN OTC DRUG LABEL
Date: 20240105

ACTIVE INGREDIENTS: CAPSAICIN 30 mg/1 1
INACTIVE INGREDIENTS: TITANIUM DIOXIDE; ZINC OXIDE; POLYBUTENE (1400 MW); PEG-20 SORBITAN STEARATE; POLYISOBUTYLENE (200000 MW); PROPYLENE CARBONATE; BUTYLATED HYDROXYTOLUENE; GLYCERYL ROSINATE; ISOPROPYL MYRISTATE; NATURAL LATEX RUBBER; CALCIUM CARBONATE

SINSINPAS CAPSAICIN HOT PATCH LARGE

Active Ingredients

Capsicum extract 0.025% as Capsaicin

Purpose

Topical Analgesic

Uses

For the temporary relief of minor aches and pains of muscles and joints associated with:

- Simple backache
- Arthritis
- Strains
- Bruises
- Sprains

Warnings

For external use only

Do not use

- on wounds or damaged skin
- with a heating pad
- if you are allergic to any ingredients of this product

When using this product

- do not use otherwise than directed
- avoid contact with eyes, mucous membranes or rashes
- do not bandage tightly
- discontinue use at least 1 hour before a bath or shower
- do not use immediately after a bath or shower

Stop use and ask a doctor if

- rash, itching, or excessive skin irritation develops
- conditions worsen
- symptoms persist for more than 7 days
- symptoms clear up and occur again within a few days

If pregnant or breast-feeding,ask a health professional before use.

Keep out of reach of children.If swallowed, get medical help or contact a Poison Control Center right away

Keep out of reach of children.If swallowed, get medical help or contact a Poison Control Center (1-800-222-1222) right away.

Directions

Adults and children 12 years of age and over:

- Clean and dry affected area
- Remove patch from film
- Apply to affected area no more than 3 to 4 times daily
- Remove patch from skin after at most 8 hours’ application

Children under 12 years of age:consult a doctor

Other information

- avoid storing product in direct sunlight
- protect product from excessive moisture

Inactive Ingredients

butyl hydroxytoluene, glyceryl rosinate, isopropryl myristate, natural rubber, polybutene, polyisobutylene, precipitated calcium carbonate, propylene carbonate, sorbitan stearate, terpene resin (quinton), terpene resin (YS resin), titanium oxide, zinc oxide

Distributed by:

SINSIN Pharm America

Brea, CA 92821